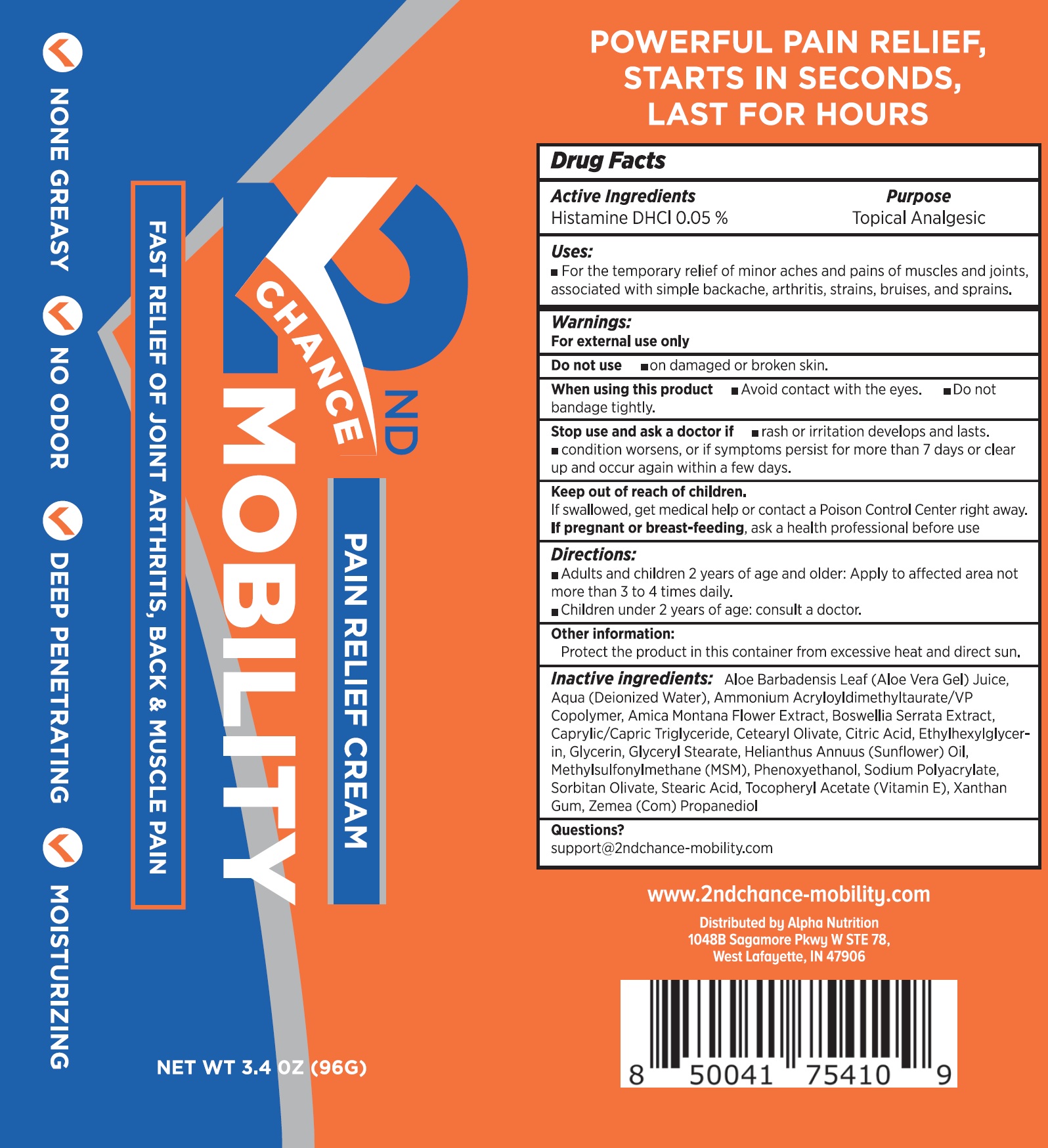 DRUG LABEL: 2nd CHANCE MOBILITY Pain Relief
NDC: 83984-441 | Form: CREAM
Manufacturer: ALPHA NUTRITION, LLC
Category: otc | Type: HUMAN OTC DRUG LABEL
Date: 20240108

ACTIVE INGREDIENTS: HISTAMINE DIHYDROCHLORIDE 0.5 mg/1 g
INACTIVE INGREDIENTS: ALOE VERA LEAF; WATER; AMMONIUM ACRYLOYLDIMETHYLTAURATE/VP COPOLYMER; ARNICA MONTANA FLOWER; INDIAN FRANKINCENSE; MEDIUM-CHAIN TRIGLYCERIDES; CETEARYL OLIVATE; CITRIC ACID MONOHYDRATE; ETHYLHEXYLGLYCERIN; GLYCERIN; GLYCERYL MONOSTEARATE; HELIANTHUS ANNUUS FLOWERING TOP; DIMETHYL SULFONE; PHENOXYETHANOL; SORBITAN OLIVATE; STEARIC ACID; .ALPHA.-TOCOPHEROL ACETATE; XANTHAN GUM; CORN

2nd CHANCE MOBILITY Pain Relief Cream

Active Ingredients

Histamine DHCL 0.05%

Purpose

Topical Analgesic

Uses:

- For the temporary relief of minor aches and pains of muscles and joints, associated with simple backache, arthritis, strains, bruises, and sprains.

Warnings:

For external use only

Do not use

- on damaged or broken skin.

When using this product

- Avoid contact with the eyes.
- Do not bandage tightly.

Stop use and ask a doctor if

- rash or irritation develops and lasts.
- condition worsens, or if symptoms persist for more than 7 days or clear up and occur again within a few days.

Keep out of reach of children.

If swallowed, get medical help or contact a Poison Control Center right away.

If pregnant or breast-feeding,

ask a health professional before use

Directions:

- Adults and children 2 years of age and older: Apply to affected area not more than 3 to 4 times daily.
- Children under 2 years of age: consult a doctor.

Other information:

Protect the product in this container from excessive heat and direct sun.

Inactive ingredients:

Aloe Barbadensis Leaf (Aloe Vera Gel) Juice, Aqua (Deionized Water), Ammonium Acryloyldimethyltaurate/VP Copolymer, Arnica Montana Flower Extract, Boswellia Serrata Extract, Caprylic/Capric Triglyceride, Cetearyl Olivate, Citric Acid, Ethylhexylglycerin, Glycerin, Glyceryl Stearate, Helianthus Annuus (Sunflower) Oil, Methylsulfonylmethane (MSM), Phenoxyethanol, Sodium Polyacrylate, Sorbitan Olivate, Stearic Acid, Tocopheryl Acetate (Vitamin E), Xanthan Gum, Zemea (Corn) Propanediol

Questions?

support@2ndchane-mobility.com